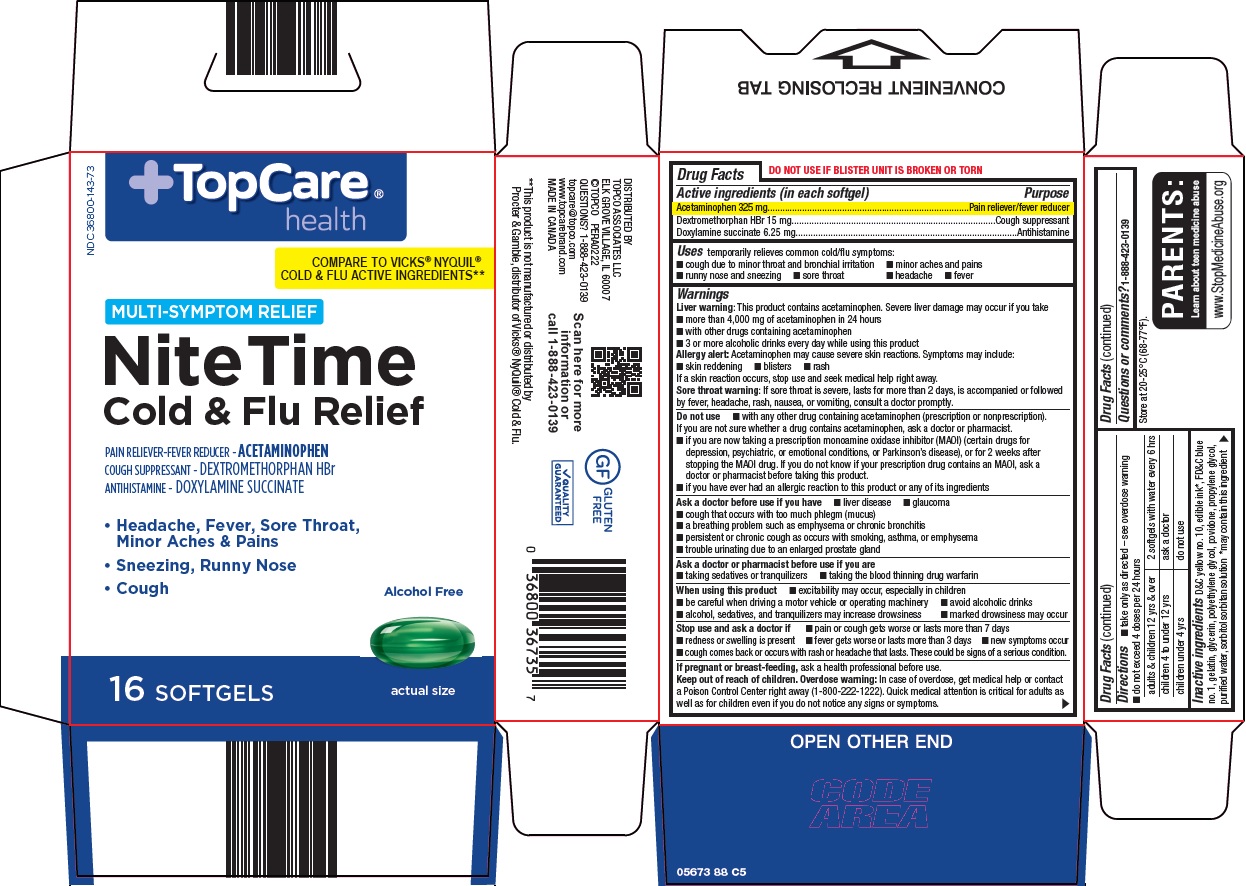 DRUG LABEL: topcare nite time cold and flu
NDC: 36800-143 | Form: CAPSULE, LIQUID FILLED
Manufacturer: Topco Associates LLC
Category: otc | Type: HUMAN OTC DRUG LABEL
Date: 20251211

ACTIVE INGREDIENTS: ACETAMINOPHEN 325 mg/1 1; DEXTROMETHORPHAN HYDROBROMIDE 15 mg/1 1; DOXYLAMINE SUCCINATE 6.25 mg/1 1
INACTIVE INGREDIENTS: D&C YELLOW NO. 10; FD&C BLUE NO. 1; GELATIN, UNSPECIFIED; GLYCERIN; POLYETHYLENE GLYCOL, UNSPECIFIED; POVIDONE, UNSPECIFIED; PROPYLENE GLYCOL; WATER; SORBITOL SOLUTION; SORBITAN

Topco Associates LLC. Nite Time Cold & Flu Drug Facts

Active ingredients (in each softgel)

Acetaminophen 325 mg

Dextromethorphan HBr 15 mg

Doxylamine succinate 6.25 mg

Purpose

Pain reliever/fever reducer

Cough suppressant

Antihistamine

Uses

temporarily relieves common cold/flu symptoms:

- cough due to minor throat and bronchial irritation
- sore throat
- headache
- minor aches and pains
- fever
- runny nose and sneezing

Warnings

Liver warning: This product contains acetaminophen. Severe liver damage may occur if you take

- more than 4,000 mg of acetaminophen in 24 hours
- with other drugs containing acetaminophen
- 3 or more alcoholic drinks every day while using this product

Allergy alert: Acetaminophen may cause severe skin reactions. Symptoms may include:

- skin reddening
- blisters
- rash

If a skin reaction occurs, stop use and seek medical help right away.

Sore throat warning: If sore throat is severe, lasts for more than 2 days, is accompanied or followed by fever, headache, rash, nausea, or vomiting, consult a doctor promptly.

Do not use

- with any other drug containing acetaminophen (prescription or nonprescription). If you are not sure whether a drug contains acetaminophen, ask a doctor or pharmacist.
- if you are now taking a prescription monoamine oxidase inhibitor (MAOI) (certain drugs for depression, psychiatric, or emotional conditions, or Parkinson’s disease), or for 2 weeks after stopping the MAOI drug. If you do not know if your prescription drug contains an MAOI, ask a doctor or pharmacist before taking this product.
- if you have ever had an allergic reaction to this product or any of its ingredients

Ask a doctor before use if you have

- liver disease
- glaucoma
- cough that occurs with too much phlegm (mucus)
- a breathing problem such as emphysema or chronic bronchitis
- persistent or chronic cough as occurs with smoking, asthma, or emphysema
- trouble urinating due to an enlarged prostate gland

Ask a doctor or pharmacist before use if you are

- taking sedatives or tranquilizers
- taking the blood thinning drug warfarin

When using this product

- excitability may occur, especially in children
- marked drowsiness may occur
- avoid alcoholic drinks
- be careful when driving a motor vehicle or operating machinery
- alcohol, sedatives, and tranquilizers may increase drowsiness

Stop use and ask a doctor if

- pain or cough gets worse or lasts more than 7 days
- fever gets worse or lasts more than 3 days
- redness or swelling is present
- new symptoms occur
- cough comes back or occurs with rash or headache that lasts. These could be signs of a serious condition.

If pregnant or breast-feeding,

ask a health professional before use.

Keep out of reach of children.

Overdose warning: In case of overdose, get medical help or contact a Poison Control Center right away (1-800-222-1222). Quick medical attention is critical for adults as well as for children even if you do not notice any signs or symptoms.

Directions

- take only as directed – see overdose warning
- do not exceed 4 doses per 24 hours

adults & children 12 yrs & over | 2 softgels with water every 6 hrs
children 4 to under 12 yrs | ask a doctor
children under 4 yrs | do not use

Inactive ingredients

D&C yellow no. 10, edible ink*, FD&C blue no. 1, gelatin, glycerin, polyethylene glycol, povidone, propylene glycol, purified water, sorbitol sorbitan solution *may contain this ingredient

Questions or comments?

1-888-423-0139

Package/Label Principal Display Panel

TopCare® health

COMPARE TO VICKS® NYQUIL® COLD & FLU ACTIVE INGREDIENTS

MULTI-SYMPTOM RELIEF

Nite Time Cold & Flu Relief

PAIN RELIEVER-FEVER REDUCER – ACETAMINOPHEN

COUGH SUPPRESSANT – DEXTROMETHORPHAN HBr

ANTIHISTAMINE – DOXYLAMINE SUCCINATE

• Headache, Fever, Sore Throat, Minor Aches & Pains

• Sneezing, Runny Nose

• Cough

Alcohol Free

16 SOFTGELS

actual size